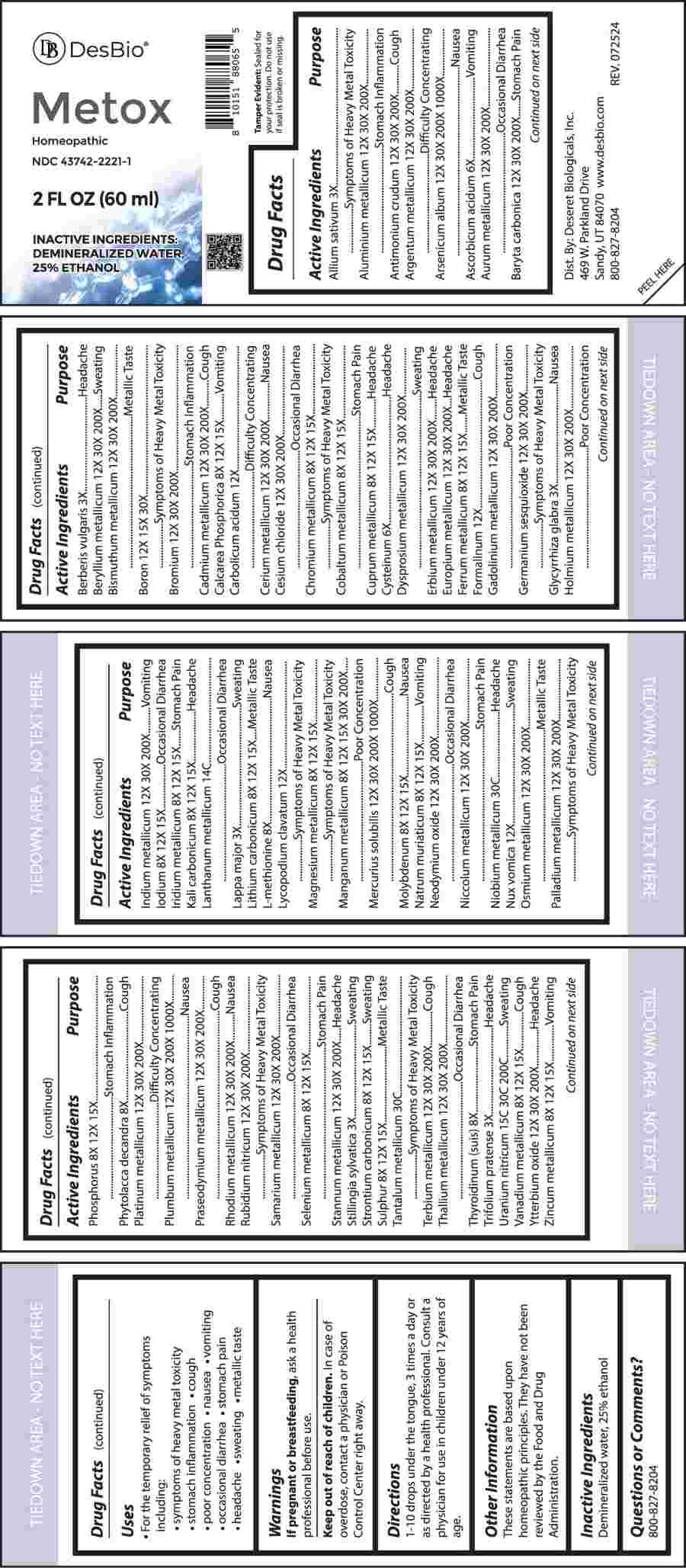 DRUG LABEL: Metox
NDC: 43742-2221 | Form: LIQUID
Manufacturer: Deseret Biologicals, Inc.
Category: homeopathic | Type: HUMAN OTC DRUG LABEL
Date: 20250117

ACTIVE INGREDIENTS: GARLIC 3 [hp_X]/1 mL; ARSENIC TRIOXIDE 1000 [hp_X]/1 mL; ASCORBIC ACID 6 [hp_X]/1 mL; BERBERIS VULGARIS ROOT BARK 3 [hp_X]/1 mL; BORON 12 [hp_X]/1 mL; PHENOL 12 [hp_X]/1 mL; CYSTEINE 6 [hp_X]/1 mL; FORMALDEHYDE SOLUTION 12 [hp_X]/1 mL; GLYCYRRHIZA GLABRA 3 [hp_X]/1 mL; LANTHANUM 14 [hp_C]/1 mL; ARCTIUM LAPPA ROOT 3 [hp_X]/1 mL; METHIONINE 8 [hp_X]/1 mL; LYCOPODIUM CLAVATUM SPORE 12 [hp_X]/1 mL; MERCURIUS SOLUBILIS 12 [hp_X]/1 mL; SODIUM CHLORIDE 8 [hp_X]/1 mL; NIOBIUM 30 [hp_C]/1 mL; STRYCHNOS NUX-VOMICA SEED 12 [hp_X]/1 mL; PHYTOLACCA AMERICANA ROOT 8 [hp_X]/1 mL; LEAD 12 [hp_X]/1 mL; STILLINGIA SYLVATICA ROOT 3 [hp_X]/1 mL; TANTALUM 30 [hp_C]/1 mL; THYROID 8 [hp_X]/1 mL; TRIFOLIUM PRATENSE FLOWER 3 [hp_X]/1 mL; URANYL NITRATE HEXAHYDRATE 15 [hp_C]/1 mL; ALUMINUM 12 [hp_X]/1 mL; ANTIMONY TRISULFIDE 12 [hp_X]/1 mL; SILVER 12 [hp_X]/1 mL; GOLD 12 [hp_X]/1 mL; BARIUM CARBONATE 12 [hp_X]/1 mL; BERYLLIUM 12 [hp_X]/1 mL; BISMUTH 12 [hp_X]/1 mL; BROMINE 12 [hp_X]/1 mL; CADMIUM 12 [hp_X]/1 mL; CERIUM 12 [hp_X]/1 mL; CESIUM CHLORIDE 12 [hp_X]/1 mL; DYSPROSIUM 12 [hp_X]/1 mL; ERBIUM 12 [hp_X]/1 mL; EUROPIUM 12 [hp_X]/1 mL; GADOLINIUM 12 [hp_X]/1 mL; GERMANIUM SESQUIOXIDE 12 [hp_X]/1 mL; HOLMIUM 12 [hp_X]/1 mL; INDIUM 12 [hp_X]/1 mL; MANGANESE 8 [hp_X]/1 mL; NEODYMIUM OXIDE 12 [hp_X]/1 mL; NICKEL 12 [hp_X]/1 mL; OSMIUM 12 [hp_X]/1 mL; PALLADIUM 12 [hp_X]/1 mL; PLATINUM 12 [hp_X]/1 mL; PRASEODYMIUM 12 [hp_X]/1 mL; RHODIUM 12 [hp_X]/1 mL; RUBIDIUM 12 [hp_X]/1 mL; SAMARIUM 12 [hp_X]/1 mL; TIN 12 [hp_X]/1 mL; TERBIUM 12 [hp_X]/1 mL; THALLIUM 12 [hp_X]/1 mL; YTTERBIUM OXIDE 12 [hp_X]/1 mL; TRIBASIC CALCIUM PHOSPHATE 8 [hp_X]/1 mL; CHROMIUM 8 [hp_X]/1 mL; COBALT 8 [hp_X]/1 mL; COPPER 8 [hp_X]/1 mL; IRON 8 [hp_X]/1 mL; IODINE 8 [hp_X]/1 mL; IRIDIUM 8 [hp_X]/1 mL; POTASSIUM CARBONATE 8 [hp_X]/1 mL; LITHIUM CARBONATE 8 [hp_X]/1 mL; MAGNESIUM 8 [hp_X]/1 mL; MOLYBDENUM 8 [hp_X]/1 mL; PHOSPHORUS 8 [hp_X]/1 mL; SELENIUM 8 [hp_X]/1 mL; STRONTIUM CARBONATE 8 [hp_X]/1 mL; SULFUR 8 [hp_X]/1 mL; VANADIUM 8 [hp_X]/1 mL; ZINC 8 [hp_X]/1 mL
INACTIVE INGREDIENTS: WATER; ALCOHOL

DRUG FACTS:

ACTIVE INGREDIENTS:

Allium Sativum 3X, Aluminum Metallicum 12X, 30X, 200X, Antimonium Crudum 12X, 30X, 200X, Argentum Metallicum 12X, 30X, 200X, Arsenicum Album 12X, 30X, 200X, 1000X, Ascorbicum Acidum 6X, Aurum Metallicum 12X, 30X, 200X, Baryta Carbonica 12X, 30X, 200X, Berberis Vulgaris 3X, Beryllium Metallicum 12X, 30X, 200X, Bismuthum Metallicum 12X, 30X, 200X, Boron 12X, 15X, 30X, Bromium 12X, 30X, 200X, Cadmium Metallicum 12X, 30X, 200X, Calcarea Phosphorica 8X, 12X, 15X, Carbolicum Acidum 12X, Cerium Metallicum 12X, 30X, 200X, Cesium Chloride 12X, 30X, 200X, Chromium Metallicum 8X, 12X, 15X, Cobaltum Metallicum 8X, 12X, 15X, Cuprum Metallicum 8X, 12X, 15X, Cysteinum 6X, Dysprosium Metallicum 12X, 30X, 200X, Erbium Metallicum 12X, 30X, 200X, Europium Metallicum 12X, 30X, 200X, Ferrum Metallicum 8X, 12X, 15X, Formalinum 12X, Gadolinium Metallicum 12X, 30X, 200X, Germanium Sesquioxide 12X, 30X, 200X, Glycyrrhiza Glabra 3X, Holmium Metallicum 12X, 30X, 200X, Indium Metallicum 12X, 30X, 200X, Iodium 8X, 12X, 15X, Iridium Metallicum 8X, 12X, 15X, Kali Carbonicum 8X, 12X, 15X, Lanthanum Metallicum 14C, Lappa Major 3X, Lithium Carbonicum 8X, 12X, 15X, L-Methionine 8X, Lycopodium Clavatum 12X, Magnesium Metallicum 8X, 12X, 15X, Manganum Metallicum 8X, 12X, 15X, 30X, 200X, Mercurius Solubilis 12X, 30X, 200X, 1000X, Molybdenum 8X, 12X, 15X, Natrum Muriaticum 8X, 12X, 15X, Neodymium Oxide 12X, 30X, 200X, Niccolum Metallicum 12X, 30X, 200X, Niobium Metallicum 30C, Nux Vomica 12X, Osmium Metallicum 12X, 30X, 200X, Palladium Metallicum 12X, 30X, 200X, Phosphorus 8X, 12X, 15X, Phytolacca Decandra 8X, Platinum Metallicum 12X, 30X, 200X, Plumbum Metallicum 12X, 30X, 200X, 1000X, Praseodymium Metallicum 12X, 30X, 200X, Rhodium Metallicum 12X, 30X, 200X, Rubidium Nitricum 12X, 30X, 200X, Samarium Metallicum 12X, 30X, 200X, Selenium Metallicum 8X, 12X, 15X, Stannum Metallicum 12X, 30X, 200X, Stillingia Sylvatica 3X, Strontium Carbonicum 8X, 12X, 15X, Sulphur 8X, 12X, 15X, Tantalum Metallicum 30C, Terbium Metallicum 12X, 30X, 200X, Thallium Metallicum 12X, 30X, 200X, Thyroidinum (Suis) 8X, Trifolium Pratense 3X, Uranium Nitricum 15C, 30C, 200C, Vanadium Metallicum 8X, 12X, 15X, Ytterbium Oxide 12X, 30X, 200X, Zincum Metallicum 8X, 12X, 15X.

PURPOSE:

Allium Sativum – Symptoms of Heavy Metal Toxicity, Aluminum Metallicum – Stomach Inflammation, Antimonium Crudum - Cough, Argentum Metallicum – Difficulty Concentrating, Arsenicum Album - Nausea, Ascorbicum Acidum - Vomiting, Aurum Metallicum – Occasional Diarrhea, Baryta Carbonica – Stomach Pain, Berberis Vulgaris - Headache, Beryllium Metallicum - Sweating, Bismuthum Metallicum – Metallic Taste, Boron – Symptoms of Heavy Metal Toxicity, Bromium – Stomach Inflammation, Cadmium Metallicum - Cough, Calcarea Phosphorica - Vomiting, Carbolicum Acidum – Difficulty Concentrating, Cerium Metallicum - Nausea, Cesium Chloride – Occasional Diarrhea, Chromium Metallicum – Symptoms of Heavy Metal Toxicity, Cobaltum Metallicum – Stomach Pain, Cuprum Metallicum - Headache, Cysteinum - Headache, Dysprosium Metallicum - Sweating, Erbium Metallicum - Headache, Europium Metallicum - Headache, Ferrum Metallicum – Metallic Taste, Formalinum - Cough, Gadolinium Metallicum – Poor Concentration, Germanium Sesquioxide – Symptoms of Heavy Metal Toxicity, Glycyrrhiza Glabra - Nausea, Holmium Metallicum – Poor Concentration, Indium Metallicum - Vomiting, Iodium – Occasional Diarrhea, Iridium Metallicum – Stomach Pain, Kali Carbonicum - Headache, Lanthanum Metallicum – Occasional Diarrhea, Lappa Major - Sweating, Lithium Carbonicum – Metallic Taste, L-Methionine - Nausea, Lycopodium Clavatum – Symptoms of Heavy Metal Toxicity, Magnesium Metallicum – Symptoms of Heavy Metal Toxicity, Manganum Metallicum – Poor Concentration, Mercurius Solubilis - Cough, Molybdenum - Nausea, Natrum Muriaticum - Vomiting, Neodymium Oxide – Occasional Diarrhea, Niccolum Metallicum – Stomach Pain, Niobium Metallicum - Headache, Nux Vomica - Sweating, Osmium Metallicum – Metallic Taste, Palladium Metallicum – Symptoms of Heavy Metal Toxicity, Phosphorus – Stomach Inflammation, Phytolacca Decandra - Cough, Platinum Metallicum – Difficulty Concentrating, Plumbum Metallicum - Nausea, Praseodymium Metallicum - Cough, Rhodium Metallicum - Nausea, Rubidium Nitricum – Symptoms of Heavy Metal Toxicity, Samarium Metallicum – Occasional Diarrhea, Selenium Metallicum – Stomach Pain, Stannum Metallicum - Headache, Stillingia Sylvatica - Sweating, Strontium Carbonicum - Sweating, Sulphur – Metallic Taste, Tantalum Metallicum – Symptoms of Heavy Metal Toxicity, Terbium Metallicum - Cough, Thallium Metallicum – Occasional Diarrhea, Thyroidinum (Suis) – Stomach Pain, Trifolium Pratense - Headache, Uranium Nitricum - Sweating, Vanadium Metallicum - Cough, Ytterbium Oxide - Headache, Zincum Metallicum - Vomiting

USES:

• For the temporary relief of symptoms including:

• symptoms of heavy metal toxicity • stomach inflammation • cough

• poor concentration • nausea • vomiting • occasional diarrhea

• stomach pain • headache • sweating • metallic taste

These statements are based upon homeopathic principles. They have not been reviewed by the Food and Drug Administration.

WARNINGS:

If pregnant or breastfeeding, ask a health professional before use.

Keep out of reach of children. In case of overdose, contact a physician or Poison Control Center right away.

Tamper Evident: Sealed for your protection. Do not use if seal is broken or missing.

KEEP OUT OF REACH OF CHILDREN:

In case of overdose, contact a physician or Poison Control Center right away.

DIRECTIONS:

1-10 drops under the tongue, 3 times a day or as directed by a health professional. Consult a physician for use in children under 12 years of age.

INACTIVE INGREDIENTS:

Demineralized water, 25% ethanol

QUESTIONS:

Dist. By: Deseret Biologicals, Inc.

469 W. Parkland Drive

Sandy, UT 84070

www.desbio.com

800-827-8204

PACKAGE LABEL DISPLAY:

DesBio

Metox

Homeopathic

NDC 43742-2221-1

2 FL OZ (60 ml)